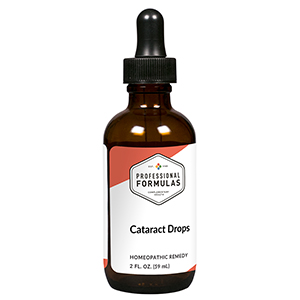 DRUG LABEL: Cataract Drops
NDC: 63083-2085 | Form: LIQUID
Manufacturer: Professional Complementary Health Formulas
Category: homeopathic | Type: HUMAN OTC DRUG LABEL
Date: 20190815

ACTIVE INGREDIENTS: EUPHRASIA STRICTA 1 [hp_X]/59 mL; BILBERRY 1 [hp_X]/59 mL; CALCIUM FLUORIDE 6 [hp_X]/59 mL; JACOBAEA MARITIMA LEAF 6 [hp_X]/59 mL; BOS TAURUS EYE 6 [hp_X]/59 mL; ZINC 6 [hp_X]/59 mL; PHOSPHORUS 8 [hp_X]/59 mL; GERMANIUM 10 [hp_X]/59 mL; CAUSTICUM 12 [hp_X]/59 mL; SILICON DIOXIDE 12 [hp_X]/59 mL; SODIUM CHLORIDE 30 [hp_X]/59 mL
INACTIVE INGREDIENTS: ALCOHOL; WATER

C85

ACTIVE INGREDIENTS

Euphrasia officinalis 1X, 3X
Vaccinium myrtillus 1X, 3X
Calcarea fluorica 6X
Cineraria maritima 6X
Eye 6X
Zincum metallicum 6X
Phosphorus 8X
Germanium 10X
Causticum 12X
Silicea 12X
Natrum muriaticum 30X

QUESTIONS

Professional Formulas

PO Box 2034 Lake Oswego, OR 97035

INDICATIONS

For the temporary relief of occasional clouded, blurred, or dim vision.*

PURPOSE

*Claims based on traditional homeopathic practice, not accepted medical evidence. Not FDA evaluated.

WARNINGS

Consult a doctor if condition worsens or if symptoms persist. Keep out of the reach of children. In case of overdose, get medical help or contact a poison control center right away. If pregnant or breastfeeding, ask a healthcare professional before use.

Keep out of the reach of children.

PREGNANCY OR BREAST FEEDING

If pregnant or breastfeeding, ask a healthcare professional before use.

DIRECTIONS

Place drops under tongue 30 minutes before/after meals. Adults and children 12 years and over: Take 10 drops up to 3 times per day. Consult a physician for use in children under 12 years of age.

OTHER INFORMATION

Tamper resistant. If seal is broken, do not use. After opening, close container tightly and store at room temperature away from heat.

INACTIVE INGREDIENTS

20% ethanol, purified water.

LABEL

Est 1985

Professional Formulas

Complementary Health

Cataract Drops

Homeopathic Remedy

2 FL. OZ. (59 mL)